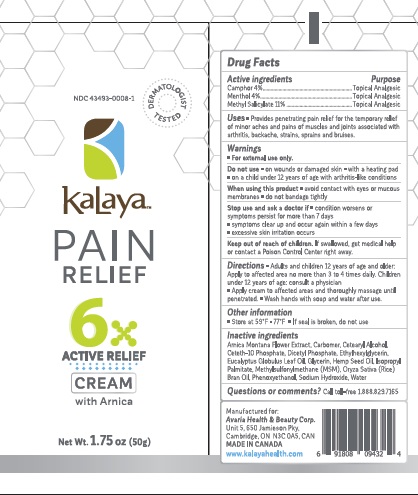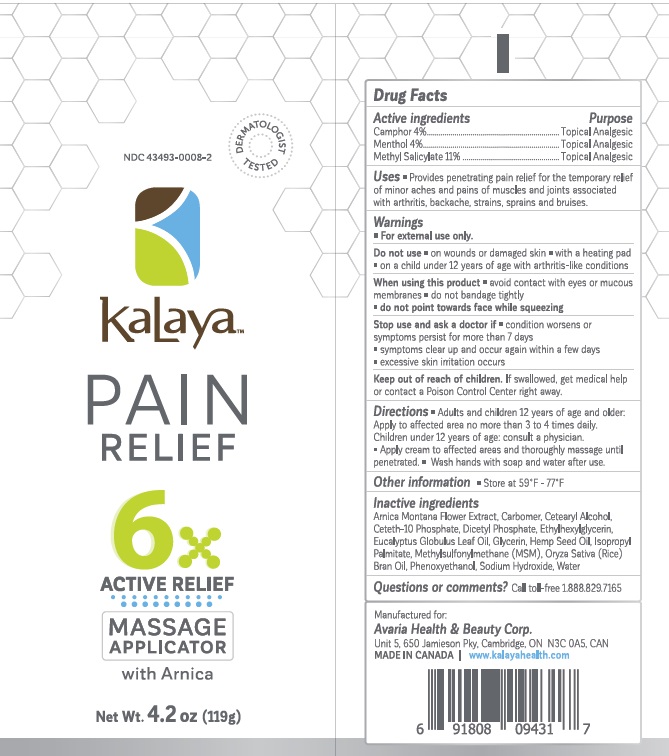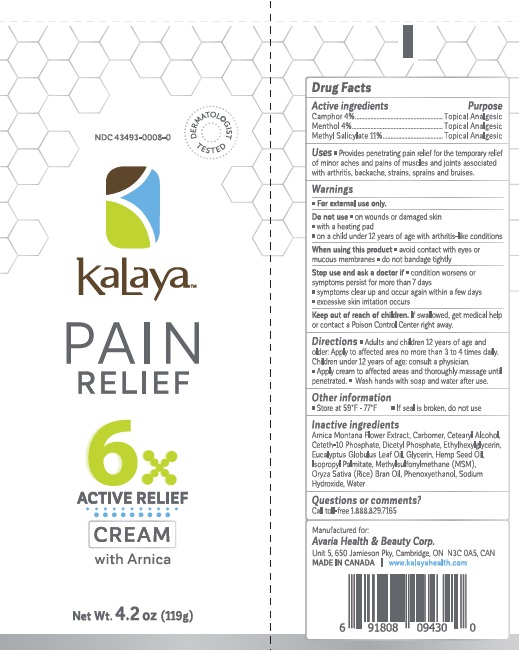 DRUG LABEL: KALAYA PAIN RELIEF 6X WITH ARNICA - Pain Relief
NDC: 43493-0008 | Form: CREAM
Manufacturer: Avaria Health & Beauty Corp
Category: otc | Type: HUMAN OTC DRUG LABEL
Date: 20251008

ACTIVE INGREDIENTS: METHYL SALICYLATE 11 g/100 g; MENTHOL 4 g/100 g; CAMPHOR (NATURAL) 4 g/100 g
INACTIVE INGREDIENTS: WATER; RICE BRAN OIL; CETYL ALCOHOL; ISOPROPYL PALMITATE; SODIUM HYDROXIDE; GLYCERIN; EUCALYPTUS OIL; ARNICA MONTANA; CARBOMER COPOLYMER TYPE A; CETETH-10 PHOSPHATE; DIHEXADECYL PHOSPHATE; DIMETHYL SULFONE; DIETHYLENE GLYCOL MONOPHENYL ETHER

Active ingredients

Camphor 4%,

Menthol 4%,

Methyl salicylate 11%

Purpose

Topical Analgesic

Uses

Penetrating pain relief for the temporary relief of minor aches and pains of muscle and joint pain associated with arthritis, backache, strains, sprains and bruises.

Warnings

• For external use only
Do not use

- on wounds or damaged skin
- with a heating pad
- on children under 12 years of age with arthritis-like conditions

When using this product

- avoid contact with eyes or mucous membranes
- do not bandage tightly
- do not point towards face while squeezing

Stop use and ask a doctor

- condition worsen or symptoms persist for more than 7 days
- symptoms clear up and occur again within a few days
- excessive skin irritation occurs

KEEP OUT OF REACH OF CHILDREN

if swallowed get medical help or contact a Poison Control Center right away.

Directions

Adults and children 12 years and over. Use no more than 3-4 times daily. Apply cream to affected areas and thoroughly massage until penetrated. Wash hands with soap and water after use.

Other information

• Store at 59°F - 77°F

Inactive ingredients

water, rice bran oil, cetyl alcohol, isopropyl palmitate, sodium hydroxide, glycerin, eucalyptus oil, arnica montana, carbomer copolymer type a, ceteth-10 phosphate, dihexadecyl phosphate, dimethyl sulfone, dimethyl sulfone, diethylene glycol monophenyl ether

Questions or comments?

Call toll-free 1.888.829.7165